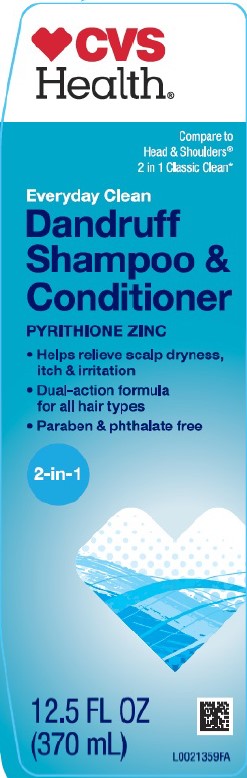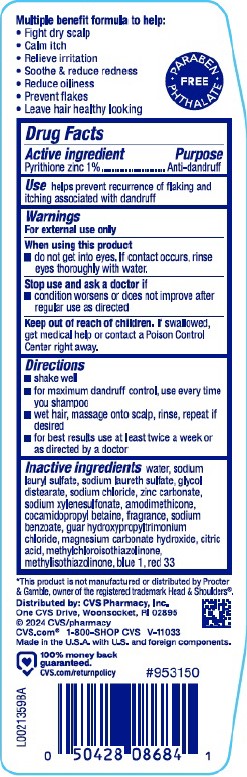 DRUG LABEL: Everyday Clean
NDC: 59779-311 | Form: SHAMPOO
Manufacturer: CVS Pharmacy, Inc.
Category: otc | Type: HUMAN OTC DRUG LABEL
Date: 20260203

ACTIVE INGREDIENTS: PYRITHIONE ZINC 10 mg/1 mL
INACTIVE INGREDIENTS: WATER; SODIUM LAURYL SULFATE; SODIUM LAURETH SULFATE; GLYCOL DISTEARATE; SODIUM CHLORIDE; ZINC CARBONATE; SODIUM XYLENESULFONATE; AMODIMETHICONE (800 CST); COCAMIDOPROPYL BETAINE; SODIUM BENZOATE; GUAR HYDROXYPROPYLTRIMONIUM CHLORIDE (1.7 SUBSTITUENTS PER SACCHARIDE); MAGNESIUM CARBONATE HYDROXIDE; CITRIC ACID MONOHYDRATE; METHYLCHLOROISOTHIAZOLINONE; METHYLISOTHIAZOLINONE; FD&C BLUE NO. 1; D&C RED NO. 33

CVS 311.007/311AK, AL, AM, AN
Everyday Clean 2 in 1 Dandruff Shampoo

Claims

Multiple benefit formula to help:

- Fight dry scalp
- Calm itch
- Relieve irritation
- Soothe and reduce redness
- Reduce oilness
- Prevent flakes
- Leave hair healthy looking

PARABEN - PHTHALATE FREE

Active ingredient

Pyrithione zinc 1%

Purpose

Anti-dandruff

Use

Helps prevent recurrence of flaking and itching associated with dandruff

Warnings

For external use only

When using this product

- do not get into eyes. If contact occurs, rinse eyes thoroughly with water.

Stop use and ask a doctor if

- condition worsens or does not improve after regular use as directed

Keep out of reach of children

If swallowed, get medical help or contact a Poison Control Center right away.

Directions

- shake well
- for maximum dandruff control, use every time you shampoo
- wet hair, massage onto scalp, rinse, repeat if desired
- for best results use at least twice a week or as directed by a doctor

inactive ingredients

water, sodium lauryl sulfate, sodium laureth sulfate, glycol distearate, sodium chloride, zinc carbonate, sodium xylenesulfonate, amodimethicone, cocamidopropyl betaine, fragrance, sodium benzoate, guar hydroxypropyltrimonium chloride, magnesium carbonate hydroxide, citric acid, methylchloroisothiazolinone, methylisothiazolinone, blue 1, red 33

Disclaimer

*This product is not manufactured or distributed by Procter & Gamble, owner of the registered trademark Head & Shoulders®.

Adverse reactions

Dstributed by: CVS Pharmacy, Inc.

One CVS Drive, Woonsocket, RI 02895

©2024 CVS/pharmacy

CVS. com 1-800-SHOP CVS

Made in the U.S.A with U.S. and foreign components.

100% money back guaranteed

CVS.com/returnpolicy

PRINCIPAL DISPLAY PANEL

CVS Health®

COMPARE TO HEAD & SHOULDERS®2 IN 1 CLASSIC CLEAN*

Everyday Clean

Dandruff Shampoo & Conditioner

PYRITHIONE XINZ

- helps relieve scalp dryness, itch & irritation
- Dual-action formula for all hair types
- paraben & phthalate free

2-in-1

12.5 FL OZ (370 mL)